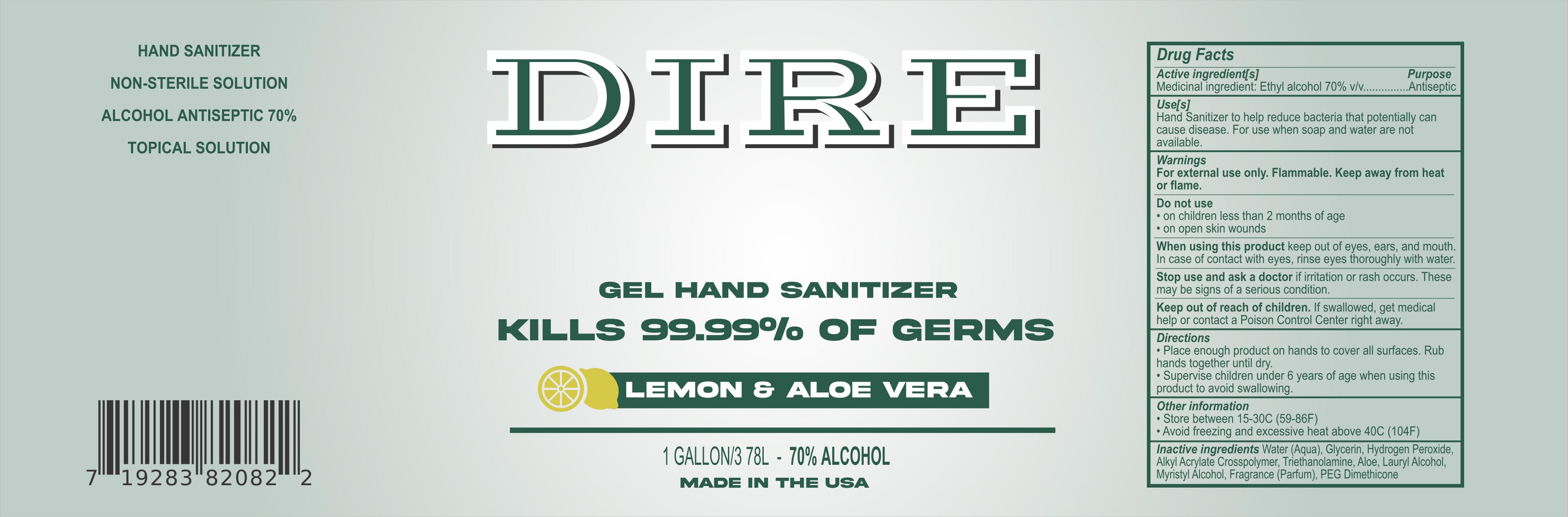 DRUG LABEL: Dire 70% Gel Hand Sanitizer - W
NDC: 74751-008 | Form: GEL
Manufacturer: Applichem, Inc
Category: otc | Type: HUMAN OTC DRUG LABEL
Date: 20201113

ACTIVE INGREDIENTS: ALCOHOL 70.6646 mL/100 mL
INACTIVE INGREDIENTS: MYRISTYL LACTATE 0.3895 mL/100 mL; ALOE VERA LEAF 0.0012 mL/100 mL; TROLAMINE 0.5177 mL/100 mL; WEST INDIAN LEMONGRASS OIL 0.0924 mL/100 mL; METHACRYLIC ACID - ETHYL ACRYLATE COPOLYMER (4500 MPA.S) 0.2087 mL/100 mL; PROPYLENE GLYCOL 0.1284 mL/100 mL; GLYCERIN 0.2805 mL/100 mL; WATER; PEG-10 DIMETHICONE (600 CST) 0.0215 mL/100 mL

Active Ingredient(s)

Alcohol 80% v/v. Purpose: Antiseptic

Purpose

Antiseptic, Hand Sanitizer

Use

Hand Sanitizer to help reduce bacteria that potentially can cause disease. For use when soap and water are not available.

Warnings

For external use only. Flammable. Keep away from heat or flame

Do not use

- on children less than 2 months of age
- on open skin wounds

When using this product keep out of eyes, ears, and mouth. In case of contact with eyes, rinse eyes thoroughly with water.
Stop use and ask a doctor if irritation or rash occurs. These may be signs of a serious condition.
Keep out of reach of children. If swallowed, get medical help or contact a Poison Control Center right away.

Stop use and ask a doctor if irritation or rash occurs. These may be signs of a serious condition.

Keep out of reach of children. If swallowed, get medical help or contact a Poison Control Center right away.

Directions

- Place enough product on hands to cover all surfaces. Rub hands together until dry.
- Supervise children under 6 years of age when using this product to avoid swallowing.

Other information

- Store between 15-30C (59-86F)
- Avoid freezing and excessive heat above 40C (104F)

Inactive ingredients

Water (Aqua), Glycerin, Hydrogen Peroxide, Alkyl Acrylate Crosspolymer, Triethanolamine, Aloe, Lauryl Alcohol, Myristyl Alcohol, Fragrance (Parfum), PEG Dimethicone

Package Label - Principal Display Panel

3780 mL NDC: 74751-008-01